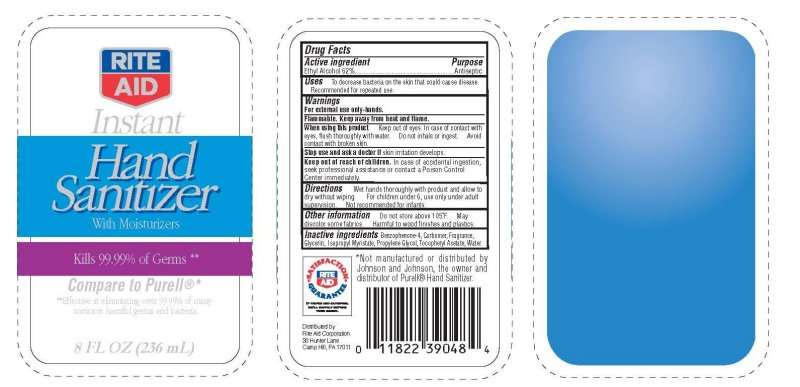 DRUG LABEL: Rite Aid Instant Hand Sanitizer
NDC: 11822-3904 | Form: GEL
Manufacturer: Rite Aid Corporation
Category: otc | Type: HUMAN OTC DRUG LABEL
Date: 20091222

ACTIVE INGREDIENTS: ALCOHOL 62 mL/100 mL
INACTIVE INGREDIENTS: WATER; GLYCERIN; CARBOMER HOMOPOLYMER TYPE C; PROPYLENE GLYCOL; ISOPROPYL MYRISTATE; ALPHA-TOCOPHEROL ACETATE; BENZOPHENONE

Rite Aid Instant Hand Sanitizer With Moisturizers

Active Ingredient Purpose

Ethyl Alchohol 62 Percent Antiseptic

Uses

To decrease bacteria on the skin that could cause disease. Recommended for repeated use.

Warnings

For external use only - hands Flammable. Keep away from heat and flame.

When using this product

Keep out of eyes. In case of contact with eyes, flush thoroughly with water. Do not inhale or ingest. Avoid contact wit broken skin.

Stop use and ask a doctor if skin irritation develops.

Keep out of reach of children.

In case of accidental ingestion, seek professional assistance or contact a Poison Control Center immediately.

Directions

Wet hands thoroughly with product and allow to dry without wiping.

For children under 6, use only under adult supervision. Not recommended for infants.

Other information:

Do not store above 105 degrees F. May discolor some fabrics. Harmful to wood finishes and plastics.

Inactive ingredients: Benzophenone-4, Carbomer, Fragrance, Glycerin,

Ispropyl Myristate, Propylene Glycol, Tocopheryl Acetate, Water

DESCRIPTION

Distributed By: Rite Aid Corporation 30 Hunter Lane Camp Hill PA 17011.

Distributed by:
Not Manufactured or distributed by Johnson and Johnson Consumer Products Company, the owner and distributor of Purell Hand Sanitizer

PACKAGE LABEL

Rite Aid

Instant Hand Sanitizer With Moisturizers

Kills 99.99 percent of germs

Effective at eliminating over 99.99 percent of many common harmful germs and bacteria.

Compare to Purell

8 Fl OZ 236 ml